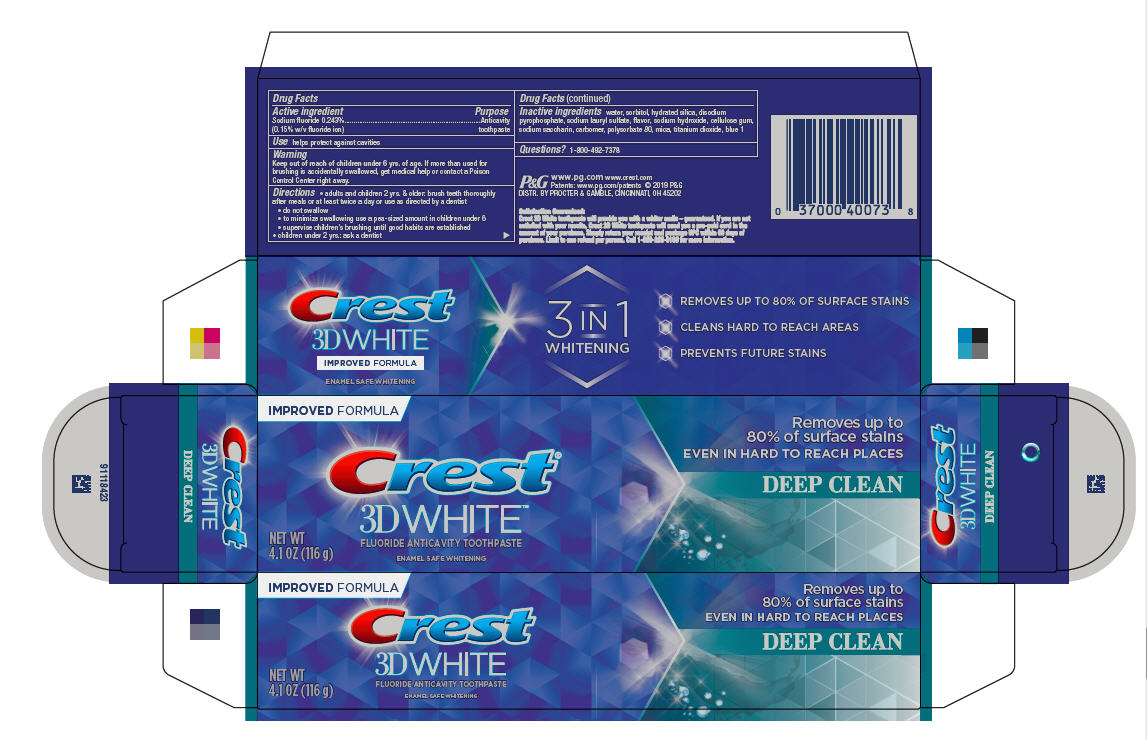 DRUG LABEL: Crest 3D White
NDC: 37000-944 | Form: PASTE, DENTIFRICE
Manufacturer: The Procter & Gamble Manufacturing Company
Category: otc | Type: HUMAN OTC DRUG LABEL
Date: 20250108

ACTIVE INGREDIENTS: SODIUM FLUORIDE 1.5 mg/1 g
INACTIVE INGREDIENTS: CARBOXYPOLYMETHYLENE; SORBITOL; WATER; HYDRATED SILICA; SODIUM ACID PYROPHOSPHATE; SODIUM LAURYL SULFATE; SODIUM HYDROXIDE; TITANIUM DIOXIDE; MICA; SACCHARIN SODIUM; POLYSORBATE 80; FD&C BLUE NO. 1; CARBOXYMETHYLCELLULOSE SODIUM

Crest® 3D White® Deep Clean

Drug Facts

Active ingredient

Sodium fluoride 0.243% (0.15% w/v fluoride ion)

Purpose

Anticavity toothpaste

Use

helps protect against cavities

Warning

Keep out of reach of children under 6 yrs. of age. If more than used for brushing is accidentally swallowed, get medical help or contact a Poison Control Center right away.

Directions

- adults and children 2 yrs. & older:
  brush teeth thoroughly after meals or at least twice a day or use as directed by a dentist
  - do not swallow
  - to minimize swallowing use a pea-sized amount in children under 6
  - supervise children's brushing until good habits are established
- children under 2 yrs.: ask a dentist

Inactive ingredients

water, sorbitol, hydrated silica, disodium pyrophosphate, sodium lauryl sulfate, flavor, sodium hydroxide, cellulose gum, sodium saccharin, carbomer, polysorbate 80, mica, titanium dioxide, blue 1

Questions?

1-800-492-7378

DISTR. BY PROCTER & GAMBLE, CINCINNATI, OH 45202

PRINCIPAL DISPLAY PANEL - 116 g Tube Carton

IMPROVED FORMULA

Crest®
3DWHITE™

FLUORIDE ANTICAVITY TOOTHPASTE

NET WT

4.1 OZ (116 g)
ENAMEL SAFE WHITENING

Removes up to 80% of surface stains

EVEN IN HARD TO REACH PLACES

DEEP CLEAN